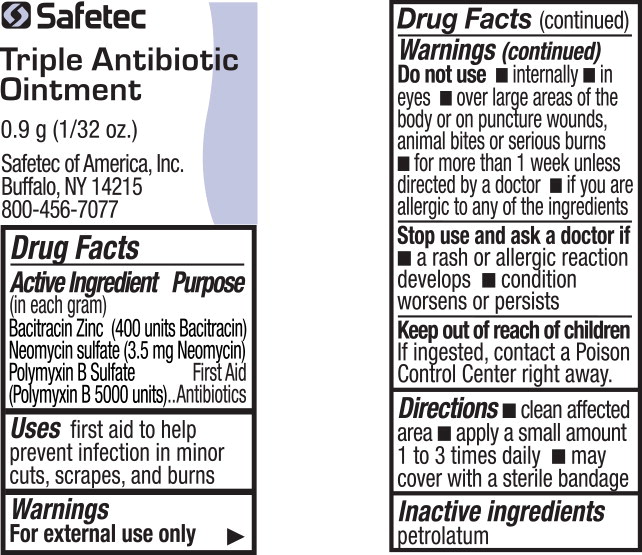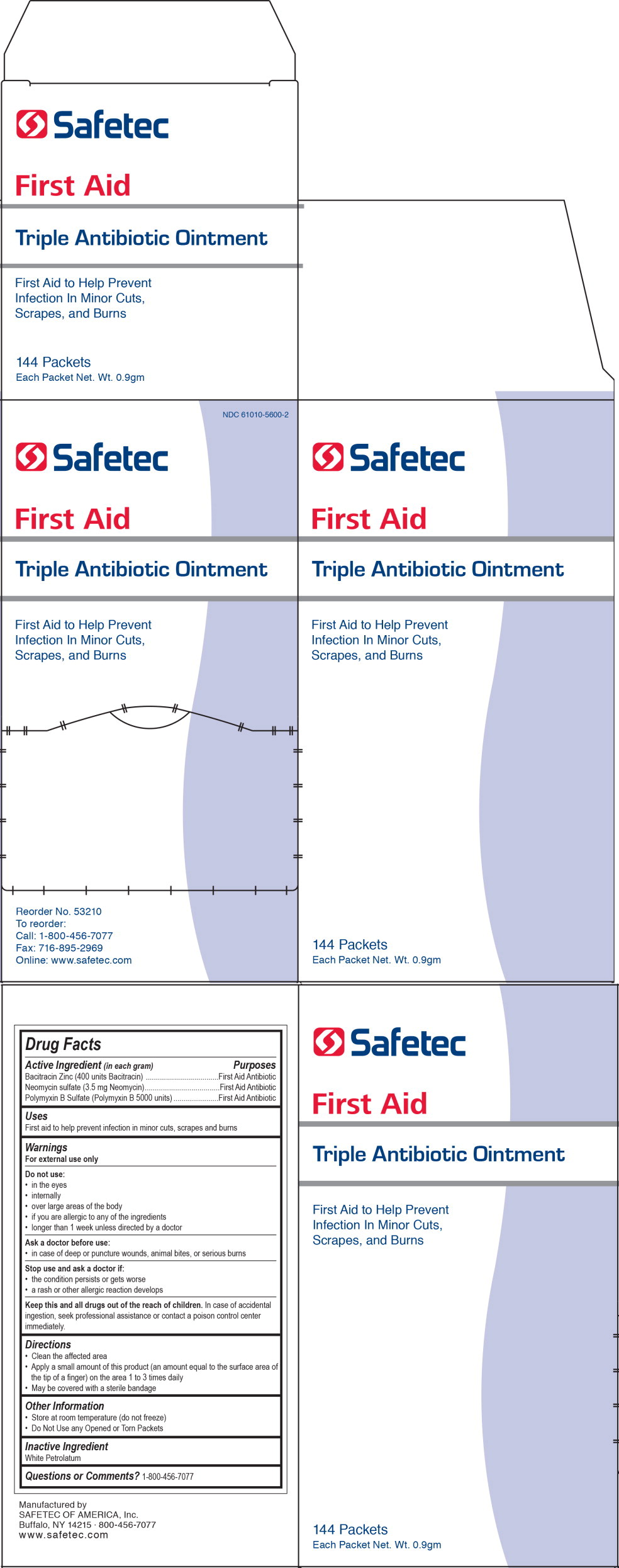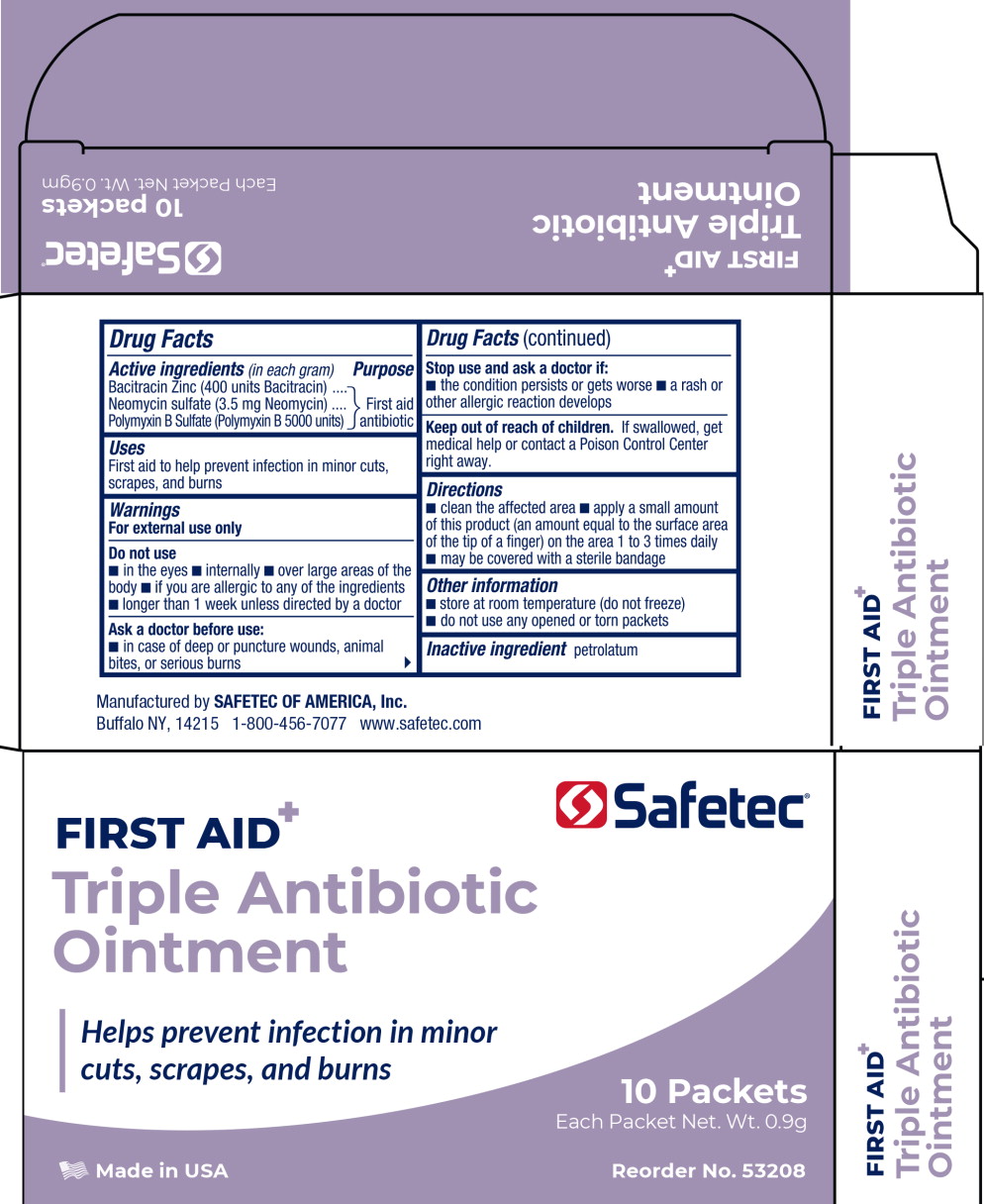 DRUG LABEL: Triple Antibiotic
NDC: 61010-5600 | Form: OINTMENT
Manufacturer: Safetec of America, Inc.
Category: otc | Type: HUMAN OTC DRUG LABEL
Date: 20240207

ACTIVE INGREDIENTS: BACITRACIN ZINC
 400 [USP'U]/1 g; NEOMYCIN SULFATE
 3.5 mg/1 g; POLYMYXIN B SULFATE
 5000 [USP'U]/1 g
INACTIVE INGREDIENTS: PETROLATUM

61010-5600, Triple Antibiotic Ointment

Drug Facts

Active Ingredient (in each gram)

Bacitracin Zinc (400 units Bacitracin)

Neomycin Sulfate (3.5 mg Neomycin)

Polymyxin B Sulfate (Polymyxin B 5000 units)

Purposes

First Aid Antibiotic

First Aid Antibiotic

First Aid Antibiotic

Uses

First aid to help prevent infection in minor cuts, scrapes and burns

Warnings

For external use only

Do not use:

- in the eyes
- internally
- over large areas of the body
- if you are allergic to any of the ingredients
- longer than 1 week unless directed by a doctor

Ask a doctor before use:

- in case of deep or puncture wounds, animal bites, or serious burns

Stop use and ask a doctor if:

- the condition persists or gets worse
- a rash or other allergic reaction develops

KEEP OUT OF REACH OF CHILDREN

Keep this and all drugs out of the reach of children.In case of accidental ingestion, seek professional assistance or contact a poison control center immediately.

Directions

- Clean the affected area
- Apply a small amount of this product (an amount equal to the surface area of the tip of a finger) on the area 1 to 3 times daily
- May be covered with a sterile bandage

Other Information

- Store at room temperature (do not freeze)
- Do Not Use any Opened or Torn Packets

Inactive Ingredient

White Petrolatum

Questions or Comments?

1-800-456-7077

PRINCIPAL DISPLAY PANEL – pouch

Safetec

Triple Antibiotic
Ointment

0.9 g (1/32 oz.)

Safetec of America, Inc.
Buffalo, NY 14215
800-456-7077

PRINCIPAL DISPLAY PANEL – 144 count box

NDC 61010-5600-2

Safetec

First Aid
Triple Antibiotic Ointment

First Aid to Help Prevent
Infection in Minor Cuts,
Scrapes, and Burns

Reorder no. 53210
To reorder:
Call: 1-800-456-7077
Fax: 716-895-2969
Online: www.safetec.com

Principal Display Panel – 10 Packet Box Label

Safetec®

First Aid
Triple Antibiotic
Ointment

Helps prevent infection in minor
cuts, scrapes, and burns

10 Packets

Each Packet Net. Wt. 0.9g

Made in USA

Reorder No. 53208